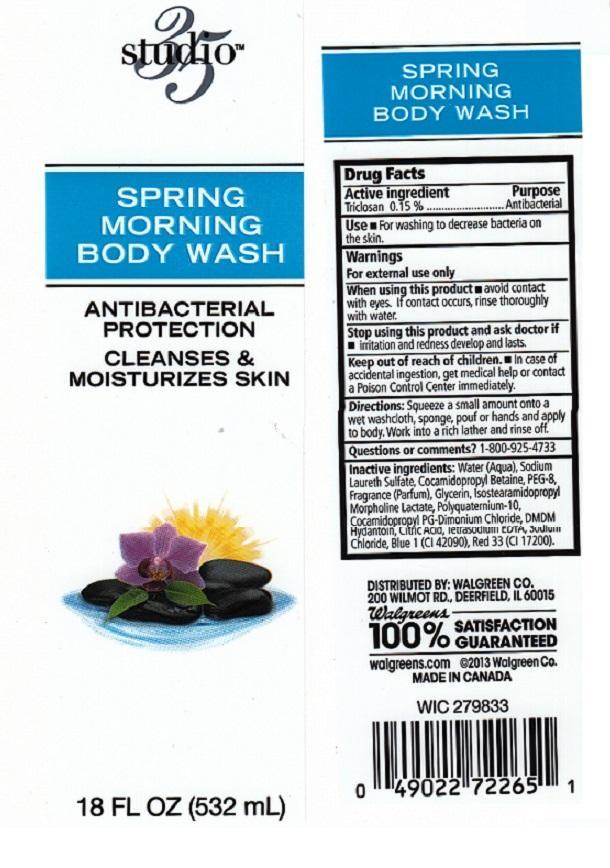 DRUG LABEL: STUDIO 35
NDC: 0363-3701 | Form: LIQUID
Manufacturer: WALGREEN COMPANY
Category: otc | Type: HUMAN OTC DRUG LABEL
Date: 20130709

ACTIVE INGREDIENTS: TRICLOSAN 1.5 mg/1 mL
INACTIVE INGREDIENTS: WATER; SODIUM LAURETH SULFATE; COCAMIDOPROPYL BETAINE; POLYETHYLENE GLYCOL 400; GLYCERIN; ISOSTEARAMIDOPROPYL MORPHOLINE LACTATE; POLYQUATERNIUM-10 (400 CPS AT 2%); COCAMIDOPROPYL PG-DIMONIUM CHLORIDE; DMDM HYDANTOIN; CITRIC ACID MONOHYDRATE; EDETATE SODIUM; SODIUM CHLORIDE; FD&C BLUE NO. 1; D&C RED NO. 33

DRUG FACTS

ACTIVE INGREDIENT

TRICLOSAN 0.15%

PURPOSE

ANTIBACTERIAL

USE

FOR WASHING TO DECREASE BACTERIA ON THE SKIN.

WARNINGS

FOR EXTERNAL USE ONLY.

WHEN USING THIS PRODUCT

AVOID CONTACT WITH EYES. IF CONTACT OCCURS, RINSE THOROUGHLY WITH WATER.

STOP USING THIS PRODUCT AND ASK DOCTOR IF

IRRITATION AND REDNESS DEVELOP AND LASTS.

KEEP OUT OF REACH OF CHILDREN

IN CASE OF ACCIDENTAL INGESTION, GET MEDICAL HELP OR CONTACT A POISON CONTROL CENTER IMMEDIATELY.

DIRECTIONS

SQUEEZE A SMALL AMOUNT ONTO A WET WASHCLOTH, SPONGE, POUF OR HANDS AND APPLY TO BODY. WORK INTO A RICH LATHER AND RINSE OFF.

QUESTIONS OR COMMENTS?

1-800-925-4733

INACTIVE INGREDIENTS:

WATER (AQUA), SODIUM LAURETH SULFATE, COCAMIDOPROPYL BETAINE, PEG-8, FRAGRANCE (PARFUM), GLYCERIN, ISPSTEARAMIDOPROPYL MORPHOLINE LACTATE, POLYQUATERNIUM-10, COCAMIDOPROPYL PG-DIMONIUM CHLORIDE, DMDM HYDANTOIN, CITRIC ACID, TETRASODIUM EDTA, SODIUM CHLORIDE, BLUE 1 (CI 42090), RED 33 (CI 17200).